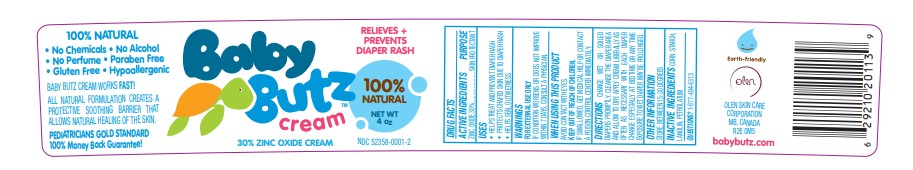 DRUG LABEL: Baby Butz
NDC: 52358-0001 | Form: CREAM
Manufacturer: Olen Skin Care Corporation
Category: otc | Type: HUMAN OTC DRUG LABEL
Date: 20231001

ACTIVE INGREDIENTS: ZINC OXIDE 17.1 g/57 g
INACTIVE INGREDIENTS: STARCH, CORN; LANOLIN; PETROLATUM

Baby Butz

Active Ingredients

Zinc Oxide 30%

Purpose

Skin Protectant

Use

- Helps treat and prevent diaper rash
- Protects chafed skin due to diaper rash
- Helps seal out wetness

Warnings

For External Use Only

ASK DOCTOR

If condition worsen or does not improve within 7 days, consult a physician.

When Using this Product

Avoid Contact with eyes.

Keep out of reach of children.

If swallowed, get medical help or contact a poison control center immediately.

Directions

Change wet or soiled diapers promptly. Cleanse the diaper area and allow to dry. Apply cream liberally as often as necessary with each diaper change especially at bedtime or any time exposure to wet diaper my be prolonged.

Other Information

Store between 15-30 degrees

Inactive Ingredients

lanolin, petrolatum

Questions?

1-877-494-4313

Principal Display Panel

Baby Butz

Cream

Relieves + Prevents

Diaper Rash

100% Natural

30% Zinc Oxide Cream

Net Wt 4 oz

NDC 52358-0001-2

OLEN SKIN CARE CORPORATION

MB, CANADA

R2E 0M5

babybutz.com